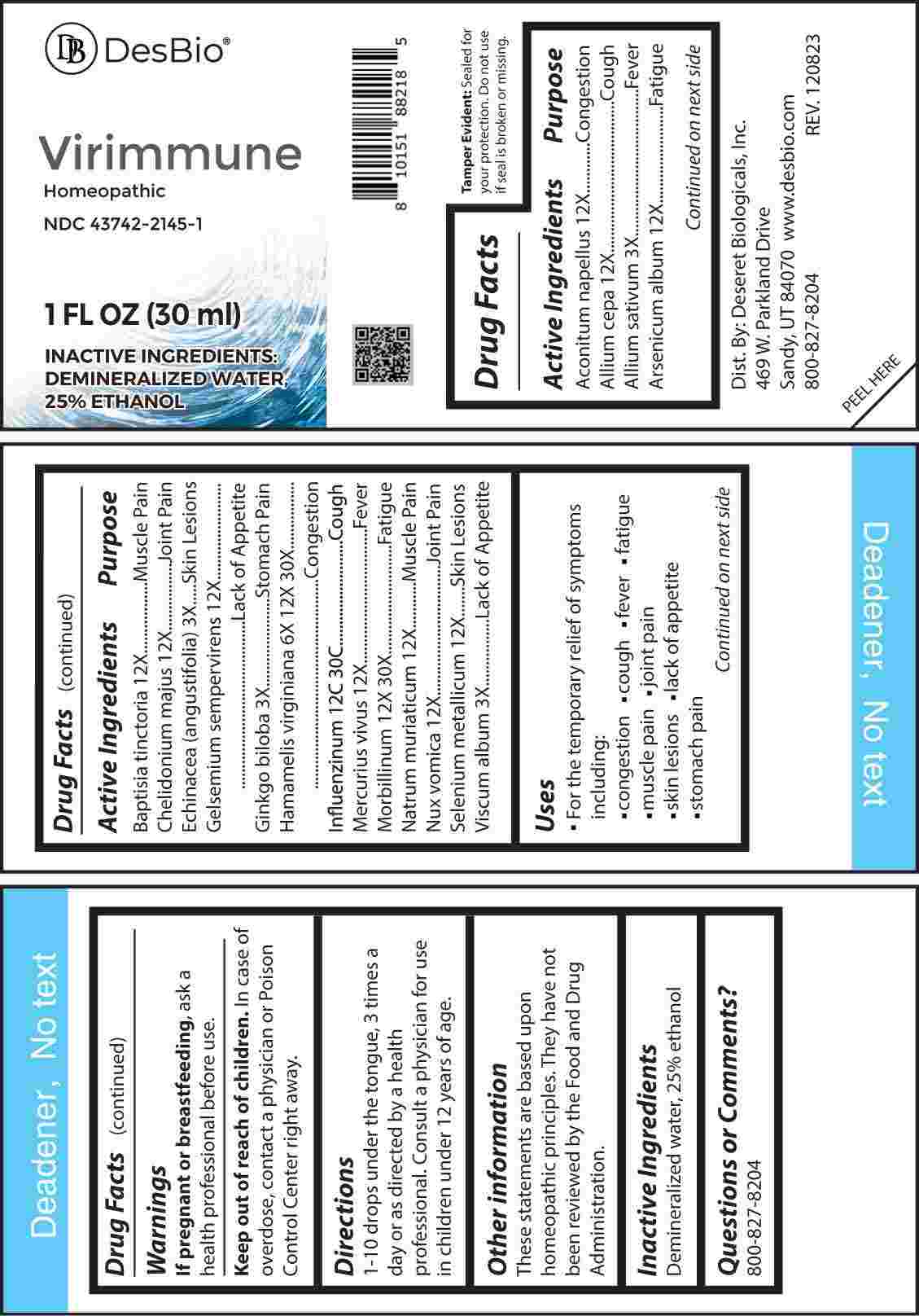 DRUG LABEL: Virimmune
NDC: 43742-2145 | Form: LIQUID
Manufacturer: Deseret Biologicals, Inc.
Category: homeopathic | Type: HUMAN OTC DRUG LABEL
Date: 20250527

ACTIVE INGREDIENTS: ACONITUM NAPELLUS WHOLE 12 [hp_X]/1 mL; ONION 12 [hp_X]/1 mL; GARLIC 3 [hp_X]/1 mL; ARSENIC TRIOXIDE 12 [hp_Q]/1 mL; BAPTISIA TINCTORIA WHOLE 12 [hp_X]/1 mL; CHELIDONIUM MAJUS WHOLE 12 [hp_X]/1 mL; ECHINACEA ANGUSTIFOLIA WHOLE 3 [hp_X]/1 mL; GELSEMIUM SEMPERVIRENS ROOT 12 [hp_X]/1 mL; GINKGO 3 [hp_X]/1 mL; HAMAMELIS VIRGINIANA ROOT BARK/STEM BARK 6 [hp_X]/1 mL; INFLUENZA A VIRUS WHOLE 12 [hp_C]/1 mL; INFLUENZA A VIRUS A/DARWIN/6/2021 (H3N2) WHOLE 12 [hp_C]/1 mL; INFLUENZA B VIRUS B/AUSTRIA/1359417/2021 BVR-26 WHOLE 12 [hp_C]/1 mL; INFLUENZA B VIRUS B/PHUKET/3073/2013 BVR-1B WHOLE 12 [hp_C]/1 mL; MERCURY 12 [hp_X]/1 mL; MEASLES VIRUS 12 [hp_X]/1 mL; SODIUM CHLORIDE 12 [hp_X]/1 mL; STRYCHNOS NUX-VOMICA SEED 12 [hp_X]/1 mL; SELENIUM 12 [hp_X]/1 mL; VISCUM ALBUM FRUITING TOP 3 [hp_X]/1 mL
INACTIVE INGREDIENTS: WATER; ALCOHOL

DRUG FACTS:

ACTIVE INGREDIENT:

Aconitum Napellus 12X, Allium Cepa 12X, Allium Sativum 3X, Arsenicum Album 12X, Baptisia Tinctoria 12X, Chelidonium Majus 12X, Echinacea (Angustifolia) 3X, Gelsemium Sempervirens 12X, Ginkgo Biloba 3X, Hamamelis Virginiana 6X, 12X, 30X, Influenzinum 12C, 30C, Mercurius Vivus 12X, Morbillinum 12X, 30X, Natrum Muriaticum 12X, Nux Vomica 12X, Selenium Metallicum 12X, Viscum Album 3X.

PURPOSE:

Aconitum Napellus - Congestion, Allium Cepa - Cough, Allium Sativum - Fever, Arsenicum Album- Fatigue, Baptisia Tinctoria – Muscle Pain, Chelidonium Majus – Joint Pain, Echinacea (Angustifolia – Skin Lesions, Gelsemium Sempervirens – Lack of Appetite, Ginkgo Biloba – Stomach Pain, Hamamelis Virginiana - Congestion, Influenzinum - Cough, Mercurius Vivus - Fever, Morbillinum - Fatigue, Natrum Muriaticum – Muscle Pain, Nux Vomica – Joint Pain, Selenium Metallicum – Skin Lesions, Viscum Album – Lack of Appetite

USES:

• For the temporary relief of the symptoms including:

• congestion • cough • fever • fatigue • muscle pain

• joint pain • skin lesions • lack of appetite • stomach pain

These statements are based upon homeopathic principles. They have not been reviewed by the Food and Drug Administration.

WARNINGS:

If pregnant or breast-feeding, ask a health professional before use.

Keep out of reach of children. In case of overdose, contact a physician or Poison Control Center right away.

Tamper Evident: Sealed for your protection. Do not use if seal is broken or missing.

KEEP OUT OF REACH OF CHILDREN:

In case of overdose, contact a physician or Poison Control Center right away.

DIRECTIONS:

1-10 drops under the tongue, 3 times a day or as directed by a health professional. Consult a physician for use in children under 12 years of age.

INACTIVE INGREDIENTS:

Demineralized water, 25% ethanol

QUESTIONS:

Dist. By: Deseret Biologicals, Inc.
469 W. Parkland Drive
Sandy, UT 84070

www.desbio.com

800-827-8204

PACKAGE LABEL DISPLAY:

DesBio

Virimmune

Homeopathic

NDC 43742-2145-1

1 FL OZ (30 ml)